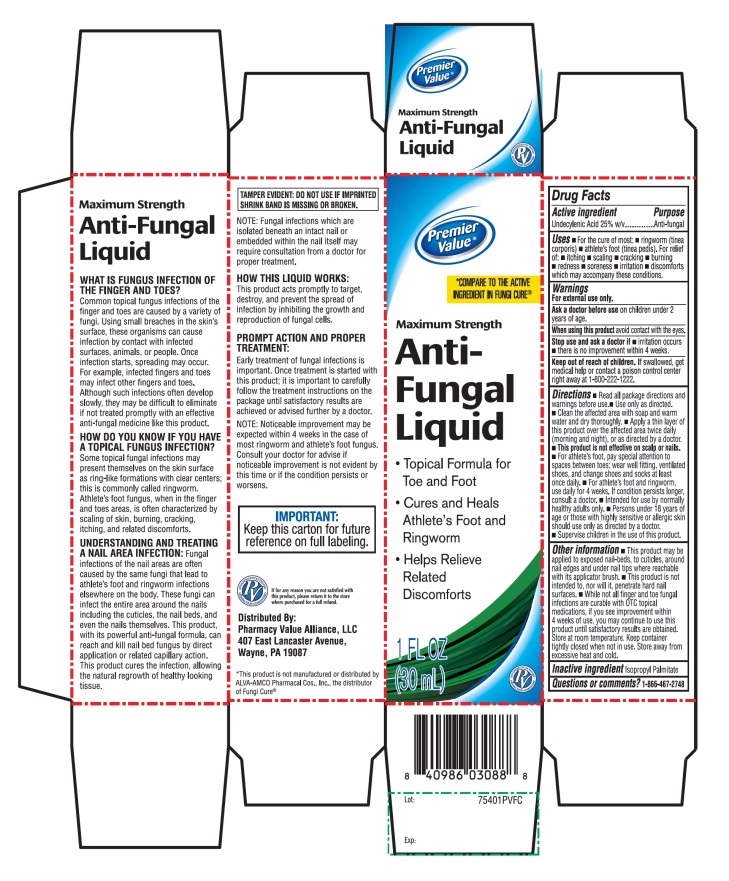 DRUG LABEL: Premier Value Antifungal
NDC: 68016-474 | Form: LIQUID
Manufacturer: PHARMACY VALUE ALLIANCE, LLC
Category: otc | Type: HUMAN OTC DRUG LABEL
Date: 20241028

ACTIVE INGREDIENTS: UNDECYLENIC ACID 25 mg/30 mL
INACTIVE INGREDIENTS: ISOPROPYL PALMITATE

Premier Value® Maximum Strength Antifungal Liquid Solution

Active ingredient

Undecylenic Acid 25%

Purpose

Anti-fungal

Uses

- For the cure of most:
- ringworm (tinea corporis)
- athlete’s foot (tinea pedis)
- itching
- scaling
- cracking
- burning
- redness
- soreness
- irritation
- discomfort

which may accompany these conditions.

Warnings

For external use only

Ask a doctor before use

On children under 2 years of age

When using this product

avoid contact with eyes

Stop use and consult a doctor if

- irritation occurs
- there is no improvement within 4 weeks

Keep out of reach of children.

If swallowed, get medical help or contact a Poison Control right away at 1-800-222-1222.

Directions

Read all warnings and directions.

- Read all package directions and warnings before use
- Use only as directed
- clean the affected area with soap and warm water and dry thoroughly
- Apply a thin layer of this product over affected area twice daily (morning and night) or as directed by a doctor.
- The brush applicator allows for easy application under nails and surrounding cuticle area.
- wear well-fitting, ventilated shoes, and change shoes and socks at least once daily
- this product is not effective on the scalp or nails
- for athlete's foot: pay special attention to spaces between toes; wear well fitting, ventilated shoes, and change shoes and socks at least once daily.
- For athlete's foot and ringworm, use daily for 4 weeks. If conditions persists longer, consult a doctor
- Intended for use by normally healthy adults only
- Persons under 18 years of age or those with highly sensitive or allergic skin should use only as directed by a doctor
- Supervise children in the use of this product

Other information

- This product may be applied to exposed nail-beds to cuticles, around nail edges and under nail tips where reachable with its applicator brush
- This product is not intended to, nor will it, penetrate hard nail surfaces
- While not all finger and toe fungal infections are curable with OTC topical medications, if you see improvement within 4 weeks of use, you may continue to use this product until satisfactory results are obtained.
- store at room temperature. Keep the container tightly closed when not in use.
- Store away from excessive heat and cold.

Inactive ingredient

Isopropyl palmitate

Questions?

Call 1-866-467-2748

Principal Display Panel

NDC 68016-474-00

COMPARE TO THE ACTIVE INGREDIENT FUNGICURE®

MAXIMUM STRENGTH
Anti-Fungal Liquid

- Topical formula for toe and foot
- Cures and Heals athlete’s foot fungus and ringworm
- Helps relieves related discomforts

1 FL OZ (30mL)

IMPORTANT: KEEP this carton for future reference on full labeling

Distributed By:

Pharmacy Value Alliance, LLC

407 East Lancaster Avenue,

Wayne, PA 19087

*This product is not manufactured or distributed by ALVA-AMCO Pharmacal Cos., Inc., the distributor of Fungi Cure®